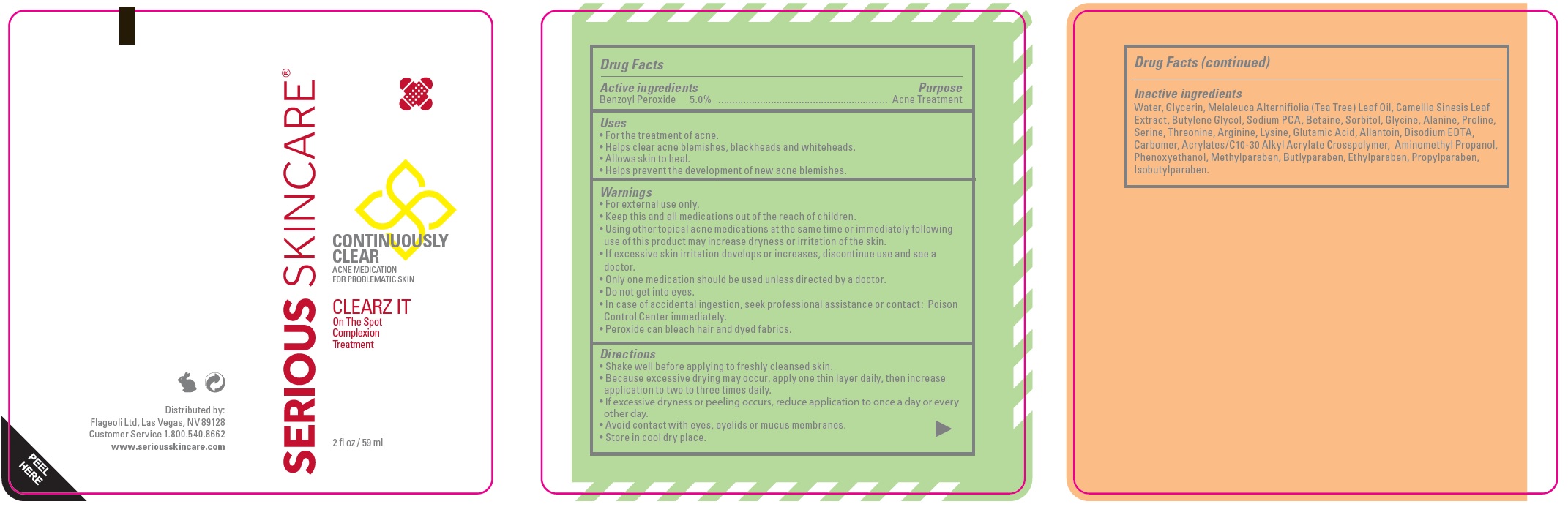 DRUG LABEL: SERIOUS SKINCARE Continuously Clear Clearz It
NDC: 53755-392 | Form: CREAM
Manufacturer: Flageoli Limited
Category: otc | Type: HUMAN OTC DRUG LABEL
Date: 20231105

ACTIVE INGREDIENTS: BENZOYL PEROXIDE 50 mg/1 mL
INACTIVE INGREDIENTS: WATER; GLYCERIN; TEA TREE OIL; GREEN TEA LEAF; BUTYLENE GLYCOL; SODIUM PYRROLIDONE CARBOXYLATE; BETAINE; SORBITOL; GLYCINE; ALANINE; PROLINE; SERINE; THREONINE; ARGININE; LYSINE; GLUTAMIC ACID; ALLANTOIN; EDETATE DISODIUM ANHYDROUS; CARBOMER HOMOPOLYMER, UNSPECIFIED TYPE; AMINOMETHYLPROPANOL; PHENOXYETHANOL; METHYLPARABEN; BUTYLPARABEN; ETHYLPARABEN; PROPYLPARABEN; ISOBUTYLPARABEN

SERIOUS SKINCARE Continuously Clear Clearz It

Active ingredients

Benzoyl Peroxide 5.0%

Purpose

Acne Treatment

Uses

• For the treatment of acne. • Helps clear acne blemishes, blackheads and whiteheads. • Allows skin to heal. • Helps prevent the development of new acne blemishes.

Warnings

• For external use only.

Keep this and all medications out of the reach of children.

• Using other topical acne medications at the same time or immediately following use of this product may increase dryness or irritation of the skin. • If excessive skin irritation develops or increases, discontinue use and see a doctor. • Only one medication should be used unless directed by a doctor. • Do not get into eyes. • In case of accidental ingestion, seek professional assistance or contact: Poison Control Center immediately. • Peroxide can bleach hair and dyed fabrics.

Directions

• Shake well before applying to freshly cleansed skin. • Because excessive drying may occur, apply one thin layer daily, then increase application to two to three times daily. • If excessive dryness or peeling occurs, reduce application to once a day or every other day. • Avoid contact with eyes, eyelids or mucus membranes. • Store in cool dry place.

Inactive ingredients

Water, Glycerin, Melaleuca Alternifiolia (Tea Tree) Leaf Oil, Camellia Sinesis Leaf Extract, Butylene Glycol, Sodium PCA, Betaine, Sorbitol, Glycine, Alanine, Proline, Serine, Threonine, Arginine, Lysine, Glutamic Acid, Allantoin, Disodium EDTA, Carbomer, Acrylates/C10-30 Alkyl Acrylate Crosspolymer, Aminomethyl Propanol, Phenoxyethanol, Methylparaben, Butlyparaben, Ethylparaben, Propylparaben, Isobutylparaben.